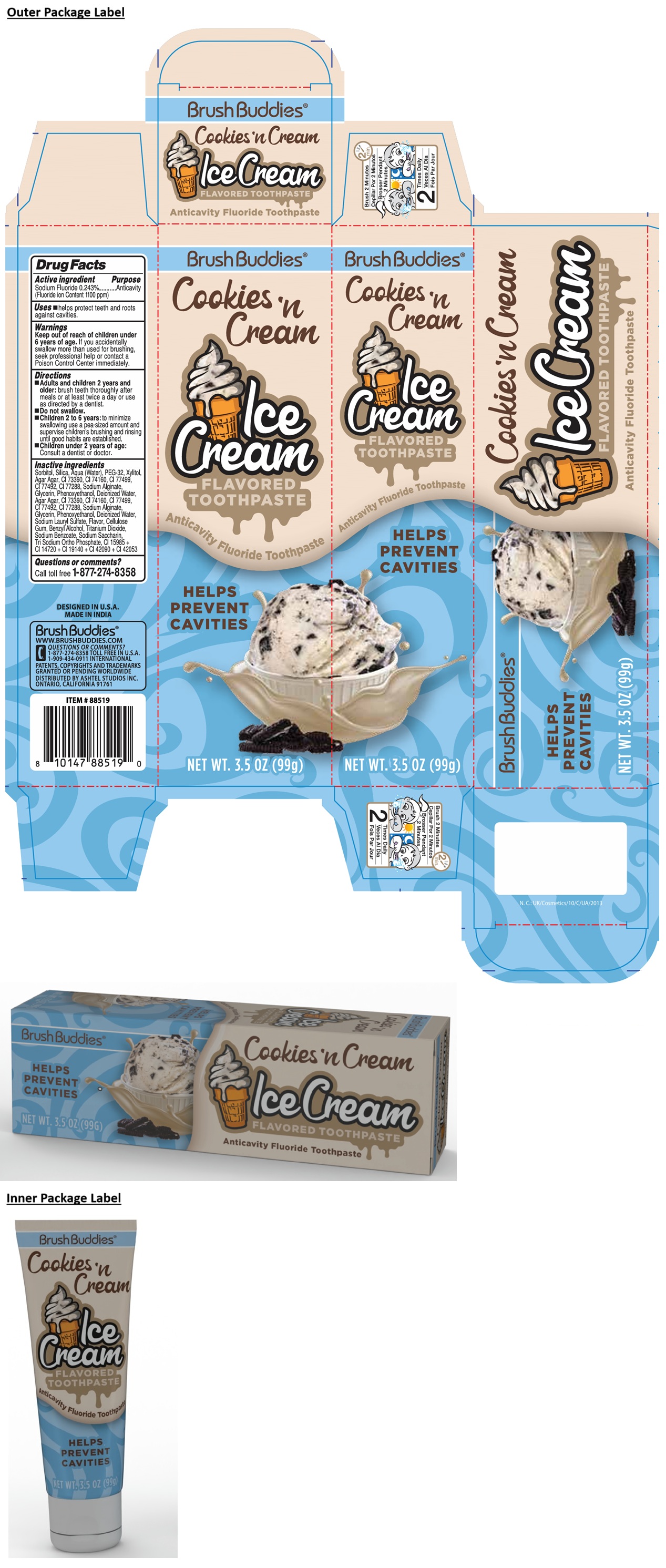 DRUG LABEL: Brush Buddies Cookies n Cream Ice Cream FLAVORED Anticavity Fluoride
NDC: 70108-237 | Form: PASTE, DENTIFRICE
Manufacturer: Ashtel Studios, Inc.
Category: otc | Type: HUMAN OTC DRUG LABEL
Date: 20250917

ACTIVE INGREDIENTS: SODIUM FLUORIDE 0.243 g/100 g
INACTIVE INGREDIENTS: SORBITOL; SILICON DIOXIDE; WATER; POLYETHYLENE GLYCOL 1600; XYLITOL; GELIDIELLA ACEROSA; D&C RED NO. 30; PHTHALOCYANINE BLUE; FERROSOFERRIC OXIDE; FERRIC OXIDE YELLOW; CHROMIC OXIDE; SODIUM ALGINATE; GLYCERIN; PHENOXYETHANOL; SODIUM LAURYL SULFATE; CARBOXYMETHYLCELLULOSE SODIUM, UNSPECIFIED; BENZYL ALCOHOL; TITANIUM DIOXIDE; SODIUM BENZOATE; SACCHARIN SODIUM; SODIUM PHOSPHATE, TRIBASIC, ANHYDROUS; FD&C YELLOW NO. 6; CARMOISINE; FD&C YELLOW NO. 5; FD&C BLUE NO. 1; FD&C GREEN NO. 3

Brush Buddies® Cookies 'n Cream Ice Cream FLAVORED Anticavity Fluoride Toothpaste

Active ingredient

Sodium Fluoride 0.243%
(Fluoride ion Content 1100 ppm)

Purpose

Anticavity

Uses

• helps protect teeth and roots against cavities.

Warnings

Keep out of reach of children under 6 years of age. If you accidentally swallow more than used for brushing, seek professional help or contact a Poison Control Center immediately.

Directions

• Adults and children 2 years and older: brush teeth thoroughly after meals or at least twice a day or use as directed by a dentist.
• Do not swallow.
• Children 2 to 6 years: to minimize swallowing use a pea-sized amount and supervise children's brushing and rinsing until good habits are established.
• Children under 2 years of age: Consult a dentist or doctor.

Inactive ingredients

Sorbitol, Silica, Aqua (Water), PEG-32, Xylitol, Agar Agar, CI 73360, CI 74160, CI 77499, CI 77492, CI 77288, Sodium Alginate, Glycerin, Phenoxyethanol, Deionized Water, Agar Agar, CI 73360, CI 74160, CI 77499, CI 77492, CI 77288, Sodium Alginate, Glycerin, Phenoxyethanol, Deionized Water, Sodium Lauryl Sulfate, Flavor, Cellulose Gum, Benzyl Alcohol, Titanium Dioxide, Sodium Benzoate, Sodium Saccharin, Tri Sodium Ortho Phosphate, CI 15985 + CI 14720 + CI 19140 + CI 42090 + CI 42053

Questions or comments?

Call toll free 1-877-274-8358

HELPS PREVENT CAVITIES

DESIGNED IN U.S.A.
MADE IN INDIA

WWW.BRUSHBUDDIES.COM
1-909-434-0911 INTERNATIONAL

PATENTS, COPYRIGHTS AND TRADEMARKS GRANTED OR PENDING WORLDWIDE
DISTRIBUTED BY ASHTEL STUDIOS INC.
ONTARIO, CALIFORNIA 91761

Brush 2 Minutes

2 Times Daily